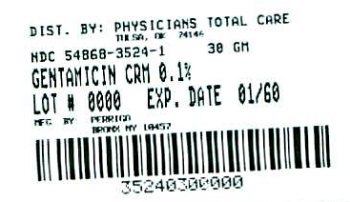 DRUG LABEL: Gentamicin Sulfate
NDC: 54868-3524 | Form: CREAM
Manufacturer: Physicians Total Care, Inc.
Category: prescription | Type: HUMAN PRESCRIPTION DRUG LABEL
Date: 20110309

ACTIVE INGREDIENTS: GENTAMICIN SULFATE 1 mg/1 g
INACTIVE INGREDIENTS: METHYLPARABEN; BUTYLPARABEN; STEARIC ACID; PROPYLENE GLYCOL MONOSTEARATE; ISOPROPYL MYRISTATE; PROPYLENE GLYCOL; POLYSORBATE 40; SORBITOL; WATER

Rx Only

DESCRIPTION

Each gram of GENTAMICIN CREAM contains gentamicin sulfate equivalent to 1 mg of gentamicin base in a cream base of: methylparaben, butylparaben, stearic acid, cerasynt PA (propylene glycol monostearate), isopropyl myristate, propylene glycol, polysorbate 40, sorbitol solution and water. Each gram of GENTAMICIN OINTMENT contains gentamicin sulfate equivalent to 1 mg of gentamicin base in a base of: Light Mineral Oil and White Petrolatum, with 0.5 mg methylparaben and 0.1 mg propylparaben as preservatives.

CLINICAL PHARMACOLOGY

GENTAMICIN, a wide spectrum antibiotic provides highly effective topical treatment in primary and secondary bacterial infections of the skin. This product may clear infections that have not responded to other topical antibiotic agents. In impetigo contagiosa and other primary skin infections, treatment with a small amount of GENTAMICIN OINTMENT AND CREAM three to four times daily usually clears the lesions promptly. In secondary skin infections, the product facilitates the treatment of the underlying dermatosis by controlling the infection. Bacteria susceptible to the action of GENTAMICIN include sensitive strains of streptococci (group A beta-hemolytic, alpha-hemolytic), Staphylococcus aureus (coagulase positive, coagulase negative, and some penicillinase-producing strains), and the gram-negative bacteria, Pseudomonas aeruginosa, Aerobacter aerogens, Escherichia coli, Proteus vulgaris and Klebsiella pneumoniae.

INDICATIONS AND USAGE

Primary skin infections: Impetigo contagiosa, superficial folliculitis, ecthyma, furunculosis, sycosis barbae, and pyoderma gangrenosum. Secondary skin infections: Infectious eczematoid dermatitis, pustular acne, pustular psoriasis, infected seborrheic dermatitis, infected contact dermatitis (including poison ivy), infected excoriations, and bacterial superinfections of fungal or viral infections. NOTE: Gentamicin is a bactericidal agent that is not effective against viruses or fungi in skin infections. It is useful in the treatment of infected skin cysts and certain other skin abscesses when preceded by incision and drainage to permit adequate contact between the antibiotic and the infecting bacteria. Good results have been obtained in the treatment of infected stasis and other skin ulcers, infected superficial burns, paronychia, infected insect bites and stings, infected lacerations and abrasions and wounds from minor surgery. Patients sensitive to neomycin can be treated with GENTAMICIN, although regular observation of patients sensitive to topical antibiotics is advisable when such patients are treated with any topical antibiotic. GENTAMICIN CREAM is recommended for wet, oozing primary infections, and greasy, secondary infections, such as pustular acne or infected seborrheic dermatitis, and where a water washable cream preparation is desired. GENTAMICIN OINTMENT helps retain moisture and has been useful in infection on dry eczematous or psoriatic skin. GENTAMICIN CREAM and OINTMENT have been used successfully in infants over one year of age as well as in adults and children.

CONTRAINDICATIONS

This product, GENTAMICIN OINTMENT AND CREAM is contraindicated in individuals with a history of sensitivity reactions to any of its components.

PRECAUTIONS

Use of topical antibiotics occasionally allows overgrowth of nonsusceptible organisms, including fungi. If this occurs, or if irritation, sensitization, or superinfection develops, treatment with GENTAMICIN should be discontinued and appropriate therapy instituted.

ADVERSE REACTIONS

In patients with dermatoses treated with GENTAMICIN, irritation (erythema and pruritus) that did not usually require discontinuance of treatment has been reported in a small percentage of cases. There was no evidence of irritation or sensitization, however, in any of these patients patch-tested subsequently with gentamicin on normal skin. Possible photosensitization has been reported in several patients but could not be elicited in these patients by reapplication of gentamicin followed by exposure to ultraviolet radiation.

DOSAGE AND ADMINISTRATION

A small amount of GENTAMICIN OINTMENT or CREAM should be applied gently to lesions three to four times a day. The area treated may be covered with a gauze dressing if desired. In impetigo contagiosa, the crusts should be removed before application of GENTAMICIN OINTMENT or CREAM to permit maximum contact between the antibiotic and the infection. Care should be exercised to avoid further contamination of the infected skin. Infected stasis ulcers have responded well to GENTAMICIN under gelatin packing.

HOW SUPPLIED

GENTAMICIN CREAM is supplied in

15 gram tube | NDC 54868-3524-0
30 gram tube | NDC 54868-3524-1

Store at controlled room temperature 15°-30°C (59°-86°F).

MANUFACTURED
BY PERRIGO
BRONX, NY 10457

1C800 RC J2

Relabeling of "Additional" barcode label by:
Physicians Total Care, Inc.
Tulsa, OK 74146

PRINCIPAL DISPLAY PANEL

GENTAMICIN CREAM

30 gram